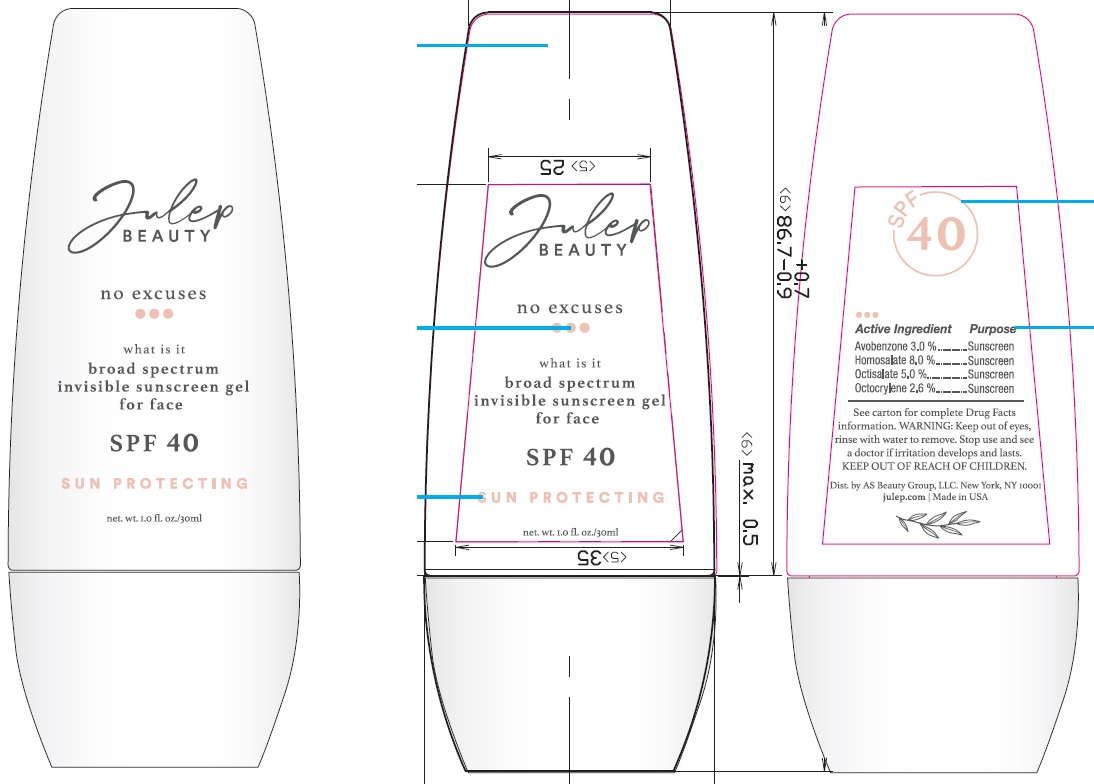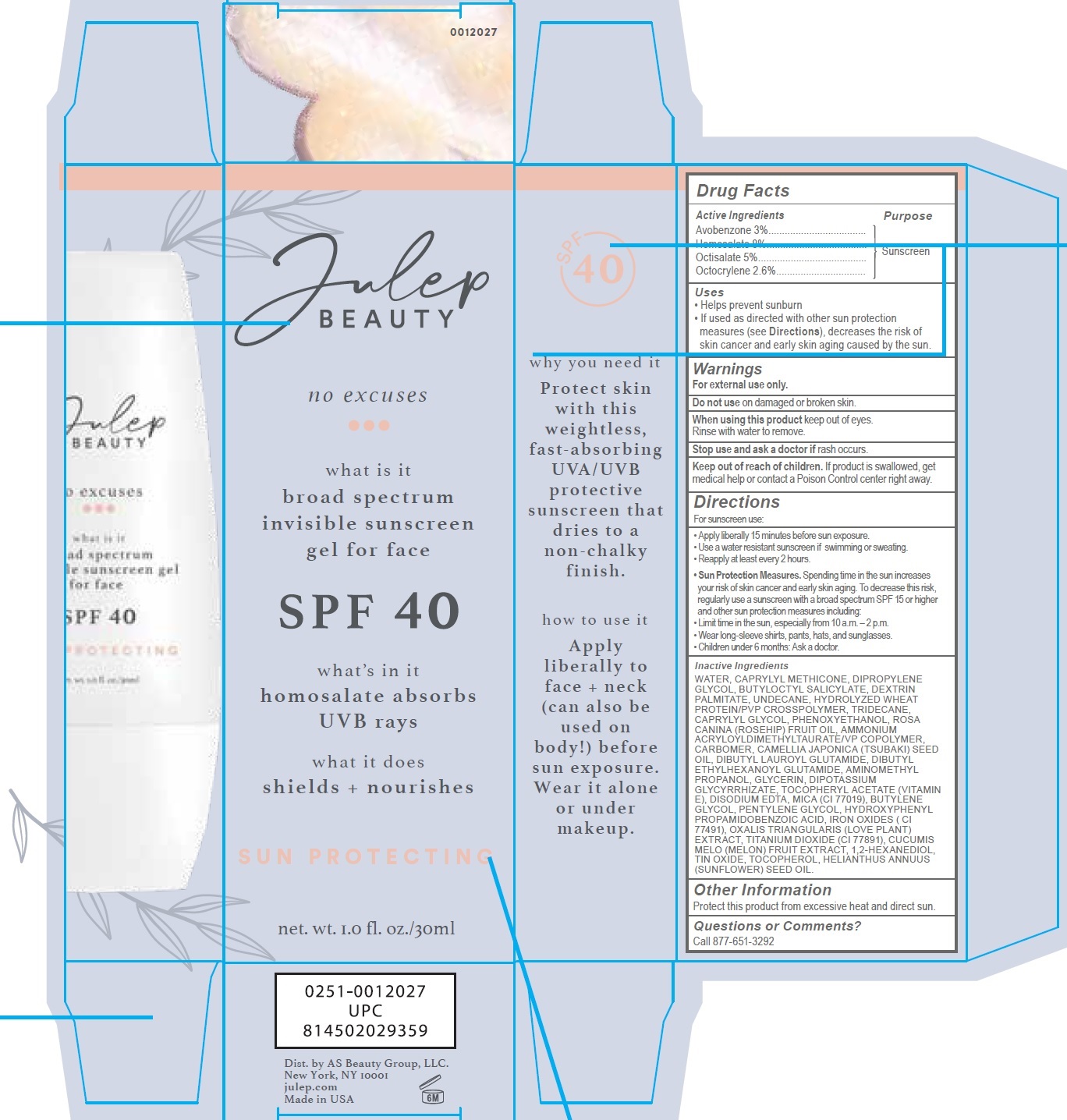 DRUG LABEL: Julep No Excuses Gel for Face SPF40
NDC: 68577-106 | Form: GEL
Manufacturer: Cosmax Usa, Corporation
Category: otc | Type: HUMAN OTC DRUG LABEL
Date: 20241226

ACTIVE INGREDIENTS: AVOBENZONE 30 mg/1 mL; HOMOSALATE 80 mg/1 mL; OCTISALATE 50 mg/1 mL; OCTOCRYLENE 26 mg/1 mL
INACTIVE INGREDIENTS: WATER; CAPRYLYL TRISILOXANE; DIPROPYLENE GLYCOL; BUTYLOCTYL SALICYLATE; UNDECANE; TRIDECANE; CAPRYLYL GLYCOL; PHENOXYETHANOL; ROSA CANINA FRUIT OIL; AMMONIUM ACRYLOYLDIMETHYLTAURATE/VP COPOLYMER; CARBOMER HOMOPOLYMER, UNSPECIFIED TYPE; CAMELLIA JAPONICA SEED OIL; DIBUTYL LAUROYL GLUTAMIDE; DIBUTYL ETHYLHEXANOYL GLUTAMIDE; AMINOMETHYLPROPANOL; GLYCERIN; GLYCYRRHIZINATE DIPOTASSIUM; .ALPHA.-TOCOPHEROL ACETATE; EDETATE DISODIUM ANHYDROUS; MICA; BUTYLENE GLYCOL; PENTYLENE GLYCOL; HYDROXYPHENYL PROPAMIDOBENZOIC ACID; FERRIC OXIDE RED; TITANIUM DIOXIDE; MUSKMELON; 1,2-HEXANEDIOL; STANNIC OXIDE; TOCOPHEROL; SUNFLOWER OIL

Julep No Excuses Gel for Face SPF40

Active Ingredients

AVOBENZONE 3%
HOMOSALATE 8%
OCTISALATE 5%

OCTOCRYLENE 2.6%

Purpose

Sunscreen

Uses

- Helps prevent sunburn.
- If used as directed with other sun protection measures (see Directions), decreases the risk of skin cancer and early skin aging caused by the sun.

Warnings

For external use only.

Do not use

on damaged or broken skin.

When using this product

keep out of eyes. Rinse with water to remove.

Stop use and ask doctor

if rash occurs.

Keep out of the reach of children.

If product is swallowed, get medical help or contact a Poison Control center right away.

Directions

For sunscreen use:

• Apply liberally 15 minutes before sun exposure.
• Use a water resistant sunscreen if swimming or sweating.
• Reapply at least every 2 hours.
• Sun Protection Measures.Spending time in the sun increases your risk of skin cancer and early skin aging. To decrease this risk, regularly use a sunscreen with a broad spectrum SPF 15 or higher and other sun protection measures including:
• Limit time in the sun, especially from 10 a.m. – 2 p.m.
• Wear long-sleeve shirts, pants, hats, and sunglasses.
• Children under 6 months: Ask a doctor.

Inactive ingredients

WATER, CAPRYLYL METHICONE, DIPROPYLENE GLYCOL, BUTYLOCTYL SALICYLATE, DEXTRIN PALMITATE, UNDECANE, HYDROLYZED WHEAT PROTEIN/PVP CROSSPOLYMER, TRIDECANE, CAPRYLYL GLYCOL, PHENOXYETHANOL, ROSA CANINA (ROSEHIP) FRUIT OIL, AMMONIUM
ACRYLOYLDIMETHYLTAURATE/VP COPOLYMER, CARBOMER, CAMELLIA JAPONICA (TSUBAKI) SEED OIL, DIBUTYL LAUROYL GLUTAMIDE, DIBUTYL
ETHYLHEXANOYL GLUTAMIDE, AMINOMETHYL PROPANOL, GLYCERIN, DIPOTASSIUM GLYCYRRHIZATE, TOCOPHERYL ACETATE (VITAMIN E), DISODIUM EDTA, MICA (CI 77019), BUTYLENE GLYCOL, PENTYLENE GLYCOL, HYDROXYPHENYL PROPAMIDOBENZOIC ACID, IRON OXIDES (CI 77491), OXALIS TRIANGULARIS (LOVE PLANT) EXTRACT, TITANIUM DIOXIDE (CI 77891), CUCUMIS MELO (MELON) FRUIT EXTRACT, 1,2-HEXANEDIOL, TIN OXIDE, TOCOPHEROL, HELIANTHUS ANNUUS (SUNFLOWER) SEED OIL.

Other Information

Protect this product from excessive heat and direct sun.

Questions or Comments?

Call 877-651-3292